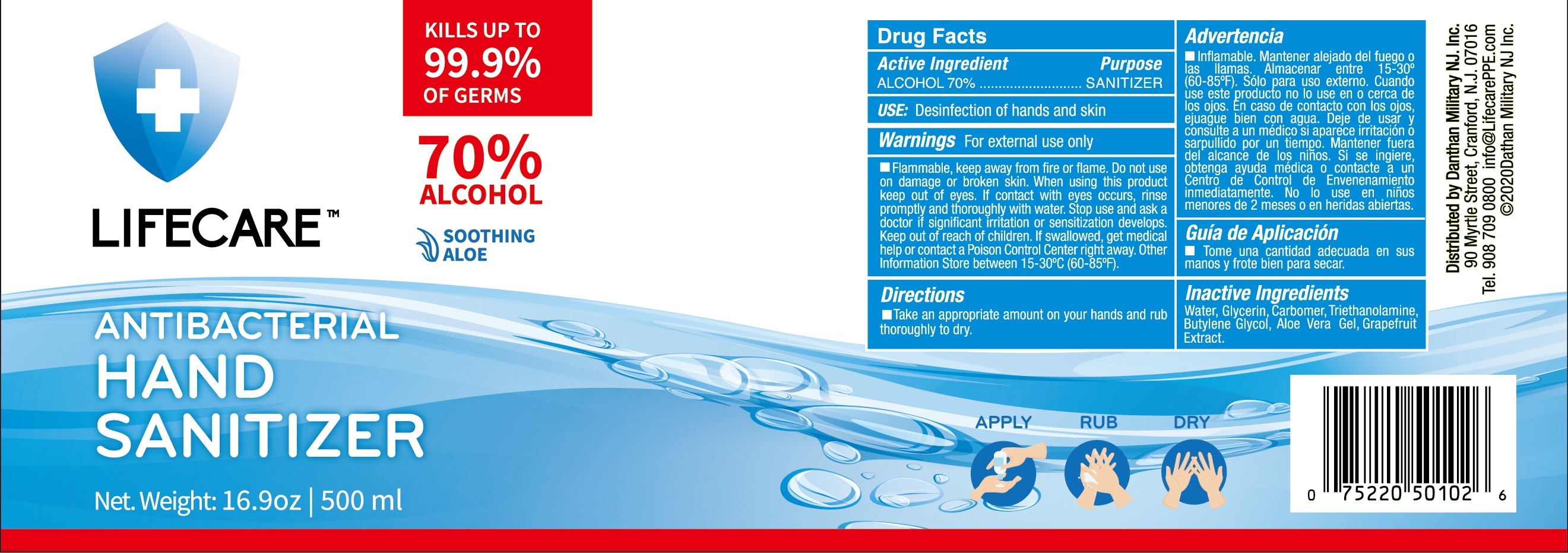 DRUG LABEL: LIFECARE ANTIBACTERIAL HAND SANITIZER
NDC: 80044-010 | Form: GEL
Manufacturer: Danthan Military NJ Inc.
Category: otc | Type: HUMAN OTC DRUG LABEL
Date: 20200811

ACTIVE INGREDIENTS: ALCOHOL 350 mL/500 mL
INACTIVE INGREDIENTS: Water; Glycerin; CARBOMER HOMOPOLYMER, UNSPECIFIED TYPE; TROLAMINE; Butylene Glycol; ALOE VERA LEAF; GRAPEFRUIT

ACTIVE INGREDIENT

ALCOHOL 70%

INACTIVE INGREDIENTS

Water, Glycerin, Carbomer, Triethanolamine, Butylene Glycol, Aloe Vera Gel, Grapefruit Extract

PURPOSE

SANITIZER

WARNINGS

For external use only
Flammable, keep away from fire or flame.
Do not use on damage or broken skin.
When using this product keep out of eyes. If contact with eyes occurs, rinse promptly and thoroughly with water.
Stop use and ask a doctor if significant irritation or sensitization develops.
Keep out of reach of children. If swallowed, get medical help or contact a Poison Control Center right away.
Other Information: Store between 15-30ºC (60-85ºF).

KEEP OUT OF REACH OF CHILDREN SECTION

If swallowed, get medical help or contact a Poison Control Center right away.

USE

Desinfection of hands and skin

Directions

Take an appropriate amount on your hands and rub thoroughly to dry.